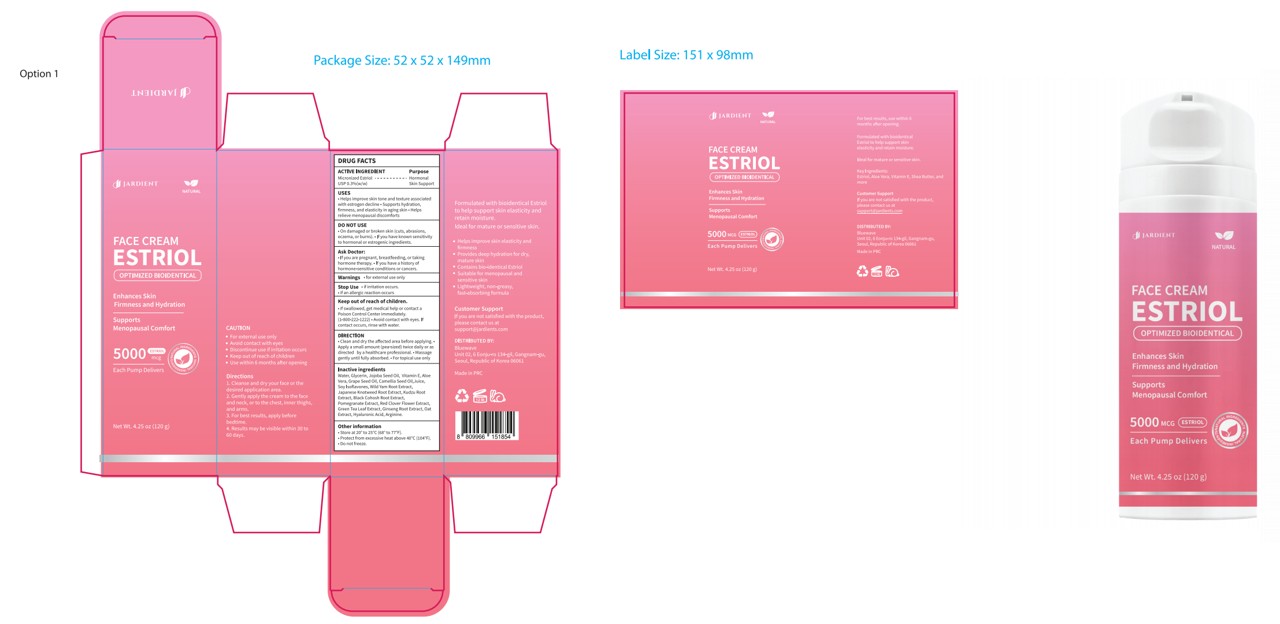 DRUG LABEL: JARDIENT
NDC: 85646-003 | Form: CREAM
Manufacturer: GLOWVERA
Category: otc | Type: HUMAN OTC DRUG LABEL
Date: 20251107

ACTIVE INGREDIENTS: ESTRIOL 0.36 g/120 g
INACTIVE INGREDIENTS: WATER; ISOFLAVONE; OAT; ARGININE; REYNOUTRIA JAPONICA ROOT; BRASSICA NAPUS SEED OIL; ALOE; TRIFOLIUM PRATENSE FLOWER; HYALURONIC ACID; PANAX GINSENG ROOT; DIOSCOREA VILLOSA ROOT; BLACK COHOSH; JOJOBA OIL; ALOE VERA LEAF JUICE; GREEN TEA LEAF; GLYCERIN; VITAMIN E POLYETHYLENE GLYCOL SUCCINATE; POMEGRANATE

Active Ingredient(s)

Micronized Estriol

Purpose

Hormonal Skin Support

Use

Helps improve skin tone and texture associated with estrogen decline . Supports hydration, firmness, and elasticity in aging skin , Helps relieve menopausal discomforts

Warnings

For external use only.

Do not use

On damaged or broken skin (cuts, abrasions ，eczema, or burns).

lfyou have known sensitivity to hormonal or estrogenic ingredients.

Ask Doctor

lf you are pregnant, breastfeeding, or takinghormone therapy.’lf you have a history ofhormone-sensitive conditions or cancers.

Stop Use

if irritation occurs.

if an allergic reaction occurs

Keep out of reach of children

If swallowed, get medical help or contact aPoison Control Centerimmediately.(1-800-222-1222)*Avoid contact with eyes.

lf contact occurs, rinse with water.

Inactive ingredients

Water, Glycerin, Jojoba Seed Oil, Vitamin E, AloeVera, Grape Seed Oil, Camellia Seed Oil,Juice,Soy lsoflavones, Wild Yam Root Extract,Japanese Knotweed Root Extract, Kudzu RootExtract, Black Cohosh Root Extract,Pomegranate Extract, Red Clover Flower Extract,Green Tea Leaf Extract, Ginseng Root Extract, OatExtract, Hyaluronic Acid, Arginine.

Other information

Store at 20° to 25°C(68° to 77°F).
Protect from excessive heat above 40°C(104°F)

Do not freeze.

DIRECTION

Clean and dry the affected area before applying.

Apply a small amount (pea-sized) twice daily or asdirected byahealthcare professional.

Massagegently until fully absorbed.·For topical use only